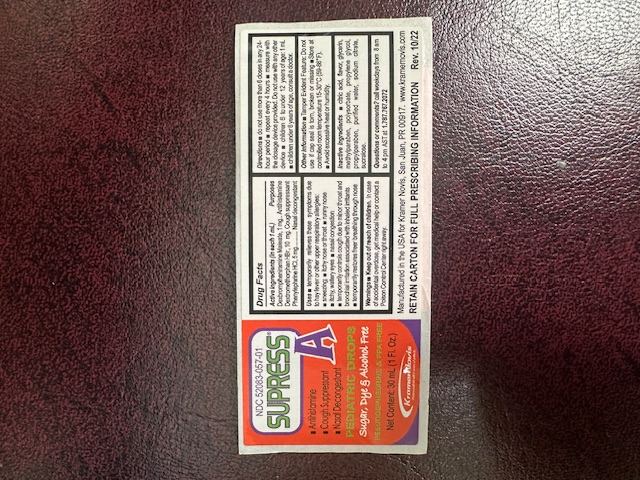 DRUG LABEL: SUPRESS A
NDC: 65852-020 | Form: SYRUP
Manufacturer: Dextrum Laboratories, Inc
Category: otc | Type: HUMAN OTC DRUG LABEL
Date: 20251013

ACTIVE INGREDIENTS: DEXBROMPHENIRAMINE MALEATE 1 mg/1 mL; PHENYLEPHRINE HYDROCHLORIDE 5 mg/1 mL; DEXTROMETHORPHAN HYDROBROMIDE 10 mg/1 mL
INACTIVE INGREDIENTS: GLYCERIN; METHYLPARABEN; CITRIC ACID; PROPYLENE GLYCOL; SODIUM CITRATE; SUCRALOSE; PROPYLPARABEN; WATER; POLYSORBATE 20

SUPRESS A

Active Ingredient Section

DEXBROMPHENIRAMINE MALEATE; DEXTROMETHORPHAN HYDROBROMIDE; PHENYLEPHRINE HYDROCHLORIDE

Inactive Ingredient Section

citric Acid, flavor, glycerin, methylparaben, polysorbate, propylene glycol, propylparaben, purified water, sodium citrate, sucralose.

Do not use section

Do not use more than 6 doses in any 24-hour period, repeat every 4 hour, measure with the dosage device provided.

Do not use with any other device, children 6 to under 12 years of ageL 1 ml, Children under 6 year of age, consult a doctor.

Keep out of reach of children section

In case of accidental overdose, get medical help or contacta Poison Control Center right away.

Purpose Section

Antihistamine, Cough suppressant, Nasal descongestant

Dosage & Administration Section

Do not use more than 6 doses in any 24-hour period, repeat every 4 hour, measure with the dosage device provided.

Do not use with any other device

children 6 to under 12 years of ageL 1 ml, Children under 6 year of age, consult a doctor.

Indication and usage Section

Use temporarity relieves these symptoms due to hay fever or other upper respiratory allergies:

- sneezing
- itchy nose or throat
- runny nose
- itchy, watery eyes
- nasal congestion
- temporarily controls cough due to minor throat and bronchial irritation associated with inhaled irritants
- temporarily restores freer breathin througt nose.

Warning Section

Keep out of reach of children. In case of overdose,, get medical help or contact Poison Control Center right away.

Question Section

Call weekdays from 8 am to 4 pm AST at 1.787.767.2072

Package Label. Principal Display Panel

NDC 52083--057-01

SUPRESS A

- Antihistamine
- Cough Suppressant
- Nasal Descongestant

PEDIATRIC DROPS

Sugar, Dye and Alcohol Free

PSEUDOEPHEDRINE & PPA FREE

Net content: 30ml (1Fl, Oz)

Kramer Novis